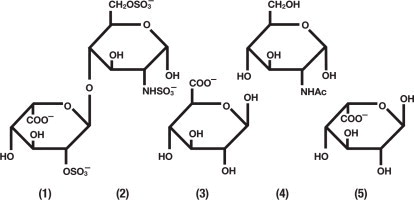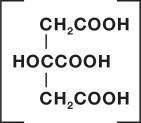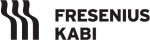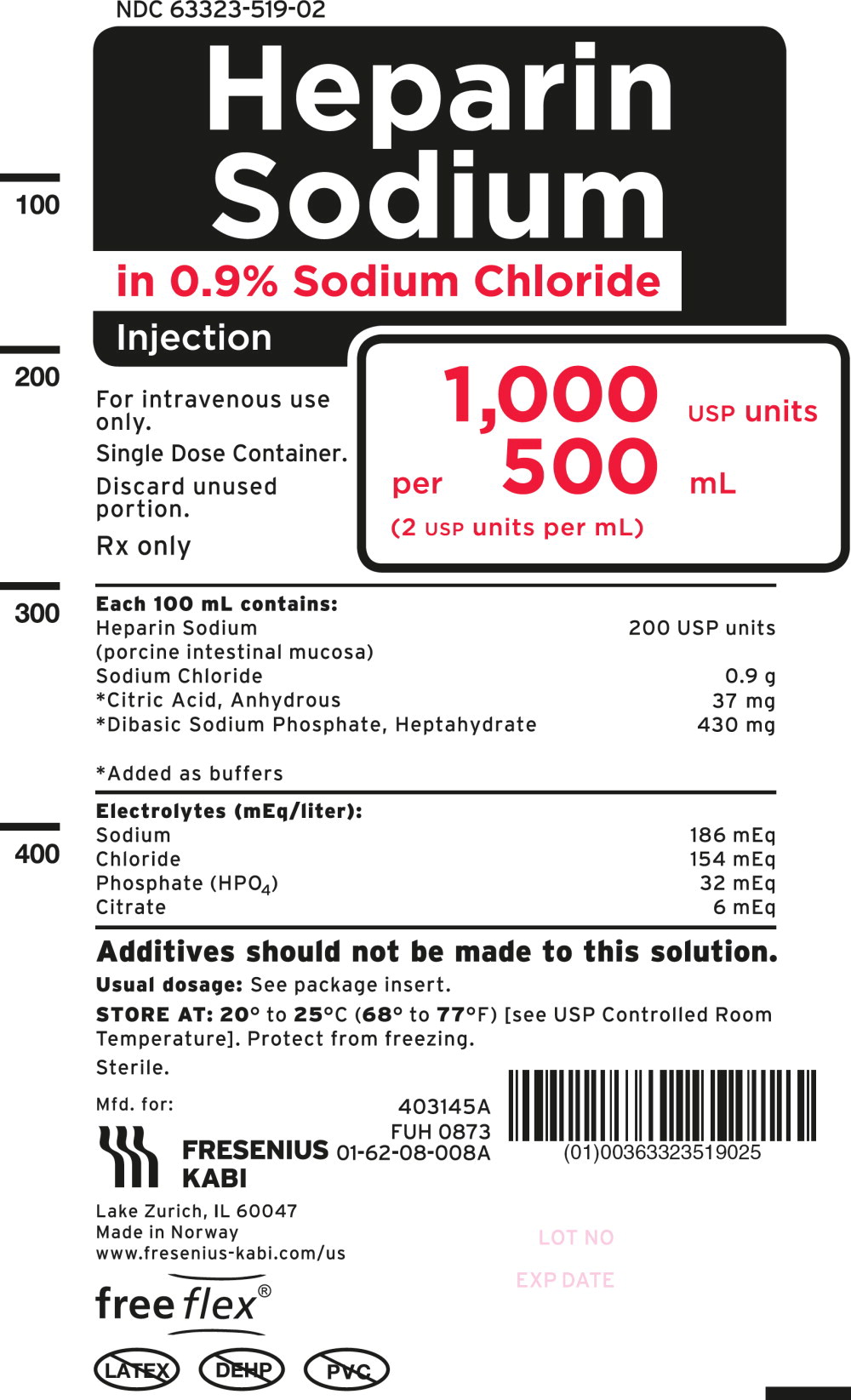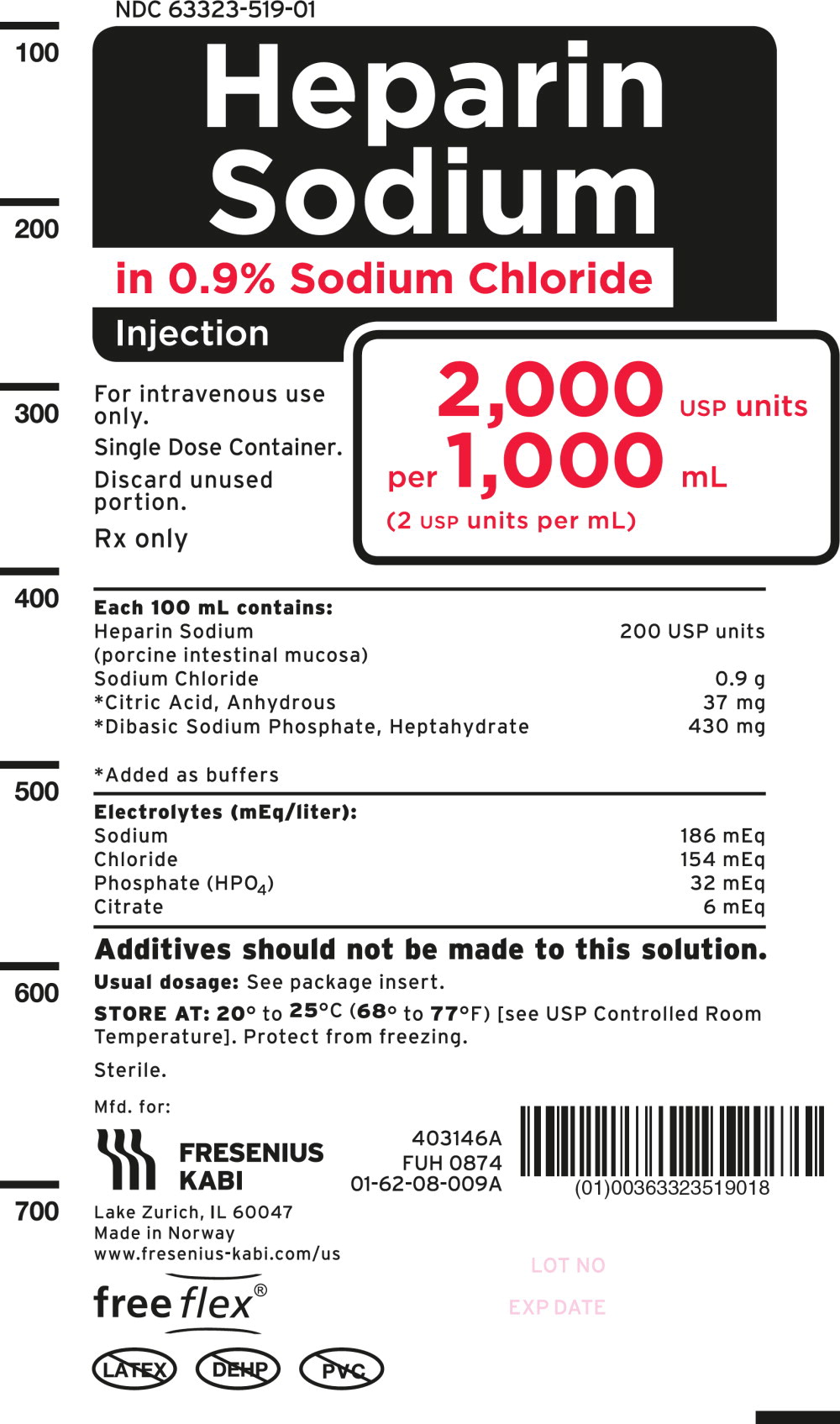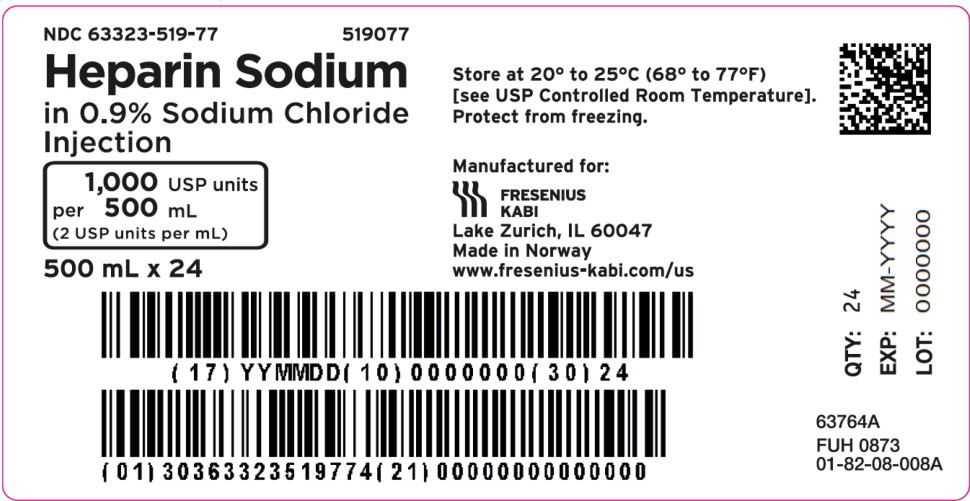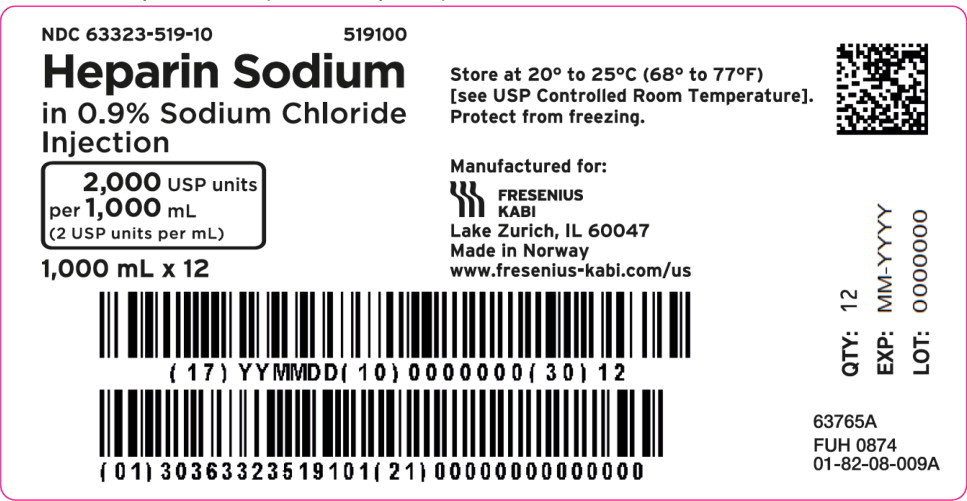 DRUG LABEL: Heparin Sodium
NDC: 63323-519 | Form: INJECTION, SOLUTION
Manufacturer: Fresenius Kabi USA, LLC
Category: prescription | Type: HUMAN PRESCRIPTION DRUG LABEL
Date: 20240430

ACTIVE INGREDIENTS: Heparin Sodium 200 [USP'U]/100 mL
INACTIVE INGREDIENTS: Anhydrous Citric Acid; Sodium Chloride; Sodium Phosphate, Dibasic, Heptahydrate

HIGHLIGHTS OF PRESCRIBING INFORMATION

These highlights do not include all the information needed to use HEPARIN SODIUM IN SODIUM CHLORIDE INJECTION safely and effectively. See full prescribing information for HEPARIN SODIUM IN SODIUM CHLORIDE INJECTION.
HEPARIN SODIUM IN SODIUM CHLORIDE INJECTION,
for intravenous use
Initial U.S. Approval: 1939

RECENT MAJOR CHANGES

Dosage and Administration (2) | 9/2019
Contraindications (4) | 9/2019
Warnings and Precautions (5) | 9/2019

1 INDICATIONS AND USAGE

HEPARIN SODIUM IN SODIUM CHLORIDE INJECTION at a concentration of 2 units/mL is indicated as an anticoagulant to maintain catheter patency. (1)

2 DOSAGE AND ADMINISTRATION

Infuse through intravenous catheter at a rate of 6 units per hour. (2.2)

3 DOSAGE FORMS AND STRENGTHS

- Injection: 1,000 USP units in Sodium Chloride per 500 mL single-dose infusion bag (2 units per mL) (3)
- Injection: 2,000 USP units in Sodium Chloride per 1,000 mL single-dose infusion bag (2 units per mL) (3)

4 CONTRAINDICATIONS

Heparin Sodium in Sodium Chloride Injection is contraindicated in patients with the following conditions: (4)

- Uncontrollable active bleeding state, except when this is due to disseminated intravascular coagulation (5.1)
- History of heparin-induced thrombocytopenia (HIT) and heparin induced thrombocytopenia with thrombosis (5.2)
- Severe thrombocytopenia (5.3)
- Known hypersensitivity to heparin or pork products (5.5, 6.1)

5 WARNINGS AND PRECAUTIONS

- Hemorrhage: Fatal hemorrhages have occurred. Monitor for signs of bleeding and manage promptly. (5.1)
- HIT and HITT: Monitor for signs and symptoms and discontinue if indicative of HIT or HITT. (5.2)
- Thrombocytopenia: Monitor platelet count during therapy; discontinue heparin if HIT or HITT is suspected. (5.3)
- Heparin Resistance: Increased resistance to heparin is frequently encountered in fever, thrombosis, thrombophlebitis, infections with thrombosing tendencies, myocardial infarction, cancer and in postsurgical patients. (5.4)
- Hypersensitivity Reactions: Use in patients with prior reactions only in life threatening situations. (5.5)
- Increased Risk of Bleeding in Older Patients, Especially Women: A higher incidence of bleeding has been reported in patients, particularly women, over 60 years of age. (5.6)
- Laboratory Tests: Periodic platelet counts, hematocrits, and tests for occult blood in stool are recommended during the entire course of heparin therapy, regardless of the route of administration. (5.7)

6 ADVERSE REACTIONS

Most common adverse reactions are: hemorrhage, thrombocytopenia, HIT and HITT, hypersensitivity, and elevations of aminotransferase levels. (6.1)

To report SUSPECTED ADVERSE REACTIONS, contact Fresenius Kabi USA, LLC at 1-800-551-7176 or FDA at 1-800-FDA-1088 or www.fda.gov/medwatch.

7 DRUG INTERACTIONS

- Drugs that interfere with platelet aggregation or drugs that counteract coagulation may induce bleeding. (7)

8 USE IN SPECIFIC POPULATIONS

- Geriatric Use: A higher incidence of bleeding has been reported in patients over 60 years of age, especially women (5.6, 8.5)

FULL PRESCRIBING INFORMATION

1 INDICATIONS AND USAGE

Heparin Sodium Injection in Sodium Chloride at a concentration of 2 units/mL is indicated as an anticoagulant to maintain catheter patency.

2 DOSAGE AND ADMINISTRATION

2.1 Preparation for Administration

Do not administer unless solution is clear and seal is intact. Parenteral drug products should be inspected visually for particulate matter and discoloration prior to administration, whenever solution and container permit.

Warning: Do not use plastic containers in series connection. Such use could result in air embolism due to residual air being drawn from the primary container before administration of the fluid from the secondary container is completed.

Do not use Heparin Sodium in Sodium Chloride Injection as a “catheter lock flush” product.

Do not admix with other drugs. Discard unused portion.

INSTRUCTIONS FOR USE for the freeflex® Bag

Leave bag in the overwrap until time of use.

The intact port cap provides visual tamper evidence. Do not use if port cap is prematurely removed.

Maintain strict aseptic technique during handling.

To Open:

1. Always inspect the bag before and after removal from the overwrap.
2. Place the bag on a clean, flat surface. Starting in the bottom corner, peel the overwrap open and remove the bag.
3. Check the bag for leaks by squeezing firmly. If leaks are found, discard the bag.
4. Do not use if the solution is cloudy or a precipitate is present.

To Prepare for Administration:

1. Immediately before connecting the infusion set, firmly grasp the BLUE infusion port cap with the arrow pointing away from the bag between index finger and thumb. Gently break off the port cap. The membrane of the infusion port is sterile, and disinfection before initial use is not necessary if proper aseptic handling technique is followed.
2. Use a non-vented infusion set or close the air-inlet on a vented set. The BLUE infusion port is compatible with spike systems produced according to ISO 8536-4, with an external spike diameter of 5.5 to 5.7 mm.
3. Close the roller clamp of the infusion set.
4. Hold the base of the BLUE infusion port and insert the spike by rotating your wrist slightly until the spike is fully inserted.
5. The port membrane contains a self-sealing septum that helps prevent leakage after removing the spike. The infusion port is not intended to be spiked more than once.
6. Hang from the hole at the top of the bag.
7. For Single Use Only. Discard unused portion.

2.2 Recommended Dosage for Maintenance of Catheter Patency

The recommended starting dose is 6 units per hour by intravenous infusion through an intravenous catheter to maintain catheter patency.

3 DOSAGE FORMS AND STRENGTHS

- Injection: 1,000 USP units per 500 mL (2 units per mL) clear solution in a single-dose infusion bag
- Injection: 2,000 USP units per 1,000 mL (2 units per mL) clear solution in a single-dose infusion bag

4 CONTRAINDICATIONS

The use of HEPARIN SODIUM IN SODIUM CHLORIDE is contraindicated in patients with the following conditions:

- Uncontrollable active bleeding state, except when this is due to disseminated intravascular coagulation [see Warnings and Precautions (5.1)]
- History of heparin-induced thrombocytopenia (HIT) and heparin-induced thrombocytopenia with thrombosis (HITT) [see Warnings and Precautions (5.2)]
- Severe thrombocytopenia [see Warnings and Precautions (5.3)]
- Known hypersensitivity to heparin or pork products (e.g., anaphylactoid reactions) [see Warnings and Precautions (5.5), Adverse Reactions (6.1)]

5 WARNINGS AND PRECAUTIONS

5.1 Hemorrhage

Avoid using heparin in the presence of major bleeding, except when the benefits of heparin therapy outweigh the potential risks.

Hemorrhage can occur at virtually any site in patients receiving heparin. Fatal hemorrhages have occurred. An unexplained fall in hematocrit or fall in blood pressure, or any other unexplained symptom should lead to serious consideration of a hemorrhagic event.

Use heparin sodium with caution in disease states in which there is increased risk of hemorrhage, including:

- Cardiovascular — Subacute bacterial endocarditis. Severe hypertension.
- Surgical — During and immediately following (a) spinal tap or spinal anesthesia or (b) major surgery, especially involving the brain, spinal cord or eye.
- Hematologic — Conditions associated with increased bleeding tendencies, such as hemophilia, thrombocytopenia and some vascular purpuras.
- Gastrointestinal — Ulcerative lesions and continuous tube drainage of the stomach or small intestine.
- Patients with hereditary antithrombin III deficiency receiving concurrent antithrombin III therapy – The anticoagulant effect of heparin is enhanced by concurrent treatment with antithrombin III (human) in patients with hereditary antithrombin III deficiency. To reduce the risk of bleeding, reduce the heparin dose during concomitant treatment with antithrombin III (human).
- Other — Menstruation, liver disease with impaired hemostasis.

5.2 Heparin-Induced Thrombocytopenia and Heparin-Induced Thrombocytopenia with Thrombosis

Heparin-induced thrombocytopenia (HIT) is a serious immune-mediated reaction. HIT occurs in patients treated with heparin and is due to the development of antibodies to a platelet Factor-4-heparin complex that induce in vivo platelet aggregation HIT may progress to the development of venous and arterial thromboses, a condition referred to as heparin-induced thrombocytopenia with thrombosis (HITT). Thrombotic events may also be the initial presentation for HITT. These serious thromboembolic events include deep vein thrombosis, pulmonary embolism, cerebral vein thrombosis, limb ischemia, stroke, myocardial infarction, mesenteric thrombosis, thrombus formation on a prosthetic cardiac valve, renal arterial thrombosis, skin necrosis, gangrene of the extremities that may lead to amputation, and possibly death.

If the platelet count falls below 100,000/mm^3 or if recurrent thrombosis develops, promptly discontinue heparin, evaluate for HIT and HITT, and, if necessary, administer an alternative anticoagulant. HIT or HITT can occur up to several weeks after the discontinuation of heparin therapy. Patients presenting with thrombocytopenia or thrombosis after discontinuation of heparin sodium should be evaluated for HIT or HITT.

HIT can occur up to several weeks after the discontinuation of heparin therapy. Patients presenting with thrombocytopenia or thrombosis after discontinuation of heparin should be evaluated for HIT.

5.3 Thrombocytopenia

Thrombocytopenia in patients receiving heparin has been reported to occur in patients receiving heparin at frequencies up to 30%. It can occur 2 to 20 days (average 5 to 9) following the onset of heparin therapy. Obtain platelet counts before and periodically during heparin therapy. If the count falls below 100,000/mm^3 or if recurrent thrombosis develops, promptly discontinue heparin, evaluate for HIT and HITT, and, if necessary, administer an alternative anticoagulant [see Warnings and Precautions (5.2)].

5.4 Heparin Resistance

Increased resistance to heparin is frequently encountered in fever, thrombosis, thrombophlebitis, infections with thrombosing tendencies, myocardial infarction, cancer and in postsurgical patients.

5.5 Hypersensitivity Reactions

Patients with documented hypersensitivity to heparin should be given the drug only in clearly life-threatening situations. Because Heparin Sodium in Sodium Chloride Injection is derived from animal tissue, it should be used with caution in patients with a history of allergy.

5.6 Increased Risk of Bleeding in Older Patients, Especially Women

A higher incidence of bleeding has been reported in patients, particularly women, over 60 years of age [see Use in Specific Populations (8.5)].

5.7 Laboratory Tests

Periodic platelet counts, hematocrits, and tests for occult blood in stool are recommended during the entire course of heparin therapy, regardless of the route of administration.

6 ADVERSE REACTIONS

The following clinically significant adverse reactions are described elsewhere in the labeling:

- Hemorrhage [see Warnings and Precautions (5.1)]
- Heparin-Induced Thrombocytopenia and Heparin-Induced thrombocytopenia with Thrombosis [see Warnings and Precautions (5.2)]
- Thrombocytopenia [see Warnings and Precautions (5.3)]
- Heparin Resistance [see Warnings and Precautions (5.4)]
- Hypersensitivity [see Warnings and Precautions (5.5)]
- Increased Risk of Bleeding in Older Patients, Especially Women [see Warnings and Precautions (5.6)]

6.1 Postmarketing Experience

The following adverse reactions have been identified during post-approval use of Heparin Sodium. Because these reactions are reported voluntarily from a population of uncertain size, it is not always possible to reliably estimate their frequency or establish a causal relationship to drug exposure.

Hemorrhage - Hemorrhage is the chief complication that may result from heparin therapy [see Warnings and Precautions (5.1)]. An overly prolonged clotting time or minor bleeding during therapy can usually be controlled by withdrawing the drug [see Overdosage (10)]. Gastrointestinal or urinary tract bleeding during anticoagulant therapy may indicate the presence of an underlying occult lesion. Bleeding can occur at any site but certain specific hemorrhagic complications may be difficult to detect:

- Adrenal hemorrhage, with resultant acute adrenal insufficiency, has occurred during anticoagulant therapy, including fatal cases.
- Ovarian (corpus luteum) hemorrhage developed in a number of women of reproductive age receiving short- or long-term anticoagulant therapy.
- Retroperitoneal hemorrhage.

HIT and HITT, including delayed onset [see Warnings and Precautions (5.2)]

Histamine-like reactions: Such reactions have been observed at the site of injections. Necrosis of the skin has been reported at the site of subcutaneous injection of heparin, occasionally requiring skin grafting.

Hypersensitivity - Generalized hypersensitivity reactions have been reported with chills, fever, and urticaria as the most usual manifestations, and asthma, rhinitis, lacrimation, headache, nausea and vomiting, and anaphylactoid reactions, including shock, occurring more rarely. Itching and burning, especially on the plantar site of the feet, may occur [see Warnings and Precautions (5.5)].

Elevations of serum aminotransferases – Significant elevations of aspartate aminotransferase (AST) and alanine aminotransferase (ALT) levels have occurred in patients who have received heparin.

Others - Osteoporosis following long-term administration of high-doses of heparin, cutaneous necrosis after systemic administration, suppression of aldosterone synthesis, delayed transient alopecia, priapism, and rebound hyperlipemia on discontinuation of heparin sodium have also been reported.

7 DRUG INTERACTIONS

7.1 Oral Anticoagulants

Heparin sodium may prolong the one-stage prothrombin time. Therefore, when heparin sodium is given with dicumarol or warfarin sodium, a period of at least 5 hours after the last intravenous dose or 24 hours after the last subcutaneous dose should elapse before blood is drawn if a valid prothrombin time is to be obtained.

7.2 Platelet Inhibitors

Drugs such as NSAIDS (including acetylsalicylic acid, ibuprofen, indomethacin, and celecoxib), dextran, phenylbutazone, thienopyridines, dipyridamole, hydroxychloroquine, glycoprotein IIv/IIa antagonists (including abciximab, eptifobatide, and tirofiban), and others that interfere with platelet-aggregation reactions (the main hemostatic defense of heparinized patients) may induce bleeding and should be used with caution in patients receiving heparin sodium. To reduce the risk of bleeding, a reduction in the dose of the antiplatelet agent or heparin is recommended.

7.3 Other Medications that May Interfere with Heparin

Digitalis, tetracyclines, nicotine or antihistamines may partially counteract the anticoagulant action of heparin sodium. Intravenous nitroglycerin administered to heparinized patients may result in a decrease of the partial thromboplastin time with subsequent rebound effect upon discontinuation of nitroglycerin. Careful monitoring of partial thromboplastin time and adjustment of heparin dosage are recommended during coadministration of heparin and intravenous nitroglycerin.

Antithrombin III (human) – The anticoagulant effect of heparin is enhanced by concurrent treatment with antithrombin III (human) in patients with hereditary antithrombin III deficiency. To reduce the risk of bleeding, a reduced dosage of heparin is recommended during treatment with antithrombin III (human).

8 USE IN SPECIFIC POPULATIONS

8.1 Pregnancy

Risk Summary

There are no available data on Heparin Sodium in Sodium Chloride Injection use in pregnant women to inform a drug-associated risk of major birth defects and miscarriage. In published reports, heparin exposure during pregnancy did not show evidence of an increased risk of adverse maternal or fetal outcomes in humans (see Data). Consider the benefits and risks of HEPARIN SODIUM IN SODIUM CHLORIDE INJECTION for the mother and possible risks to the fetus when prescribing HEPARIN SODIUM IN SODIUM CHLORIDE INJECTION.

The estimated background risk of major birth defects and miscarriage for the indicated population is unknown. All pregnancies have a background risk of birth defect, loss, or other adverse outcomes. In the U.S. general population, the estimated background risk of major birth defects and miscarriage in clinically recognized pregnancies is 2-4% and 15-20%, respectively.

Data

Human Data

The maternal and fetal outcomes associated with uses of heparin via various dosing methods and administration routes during pregnancy have been investigated in numerous studies. These studies generally reported normal deliveries with no maternal or fetal bleeding and no other complications.

Animal Data

In a published study conducted in rats and rabbits, pregnant animals received heparin intravenously during organogenesis at a dose of 10,000 USP units/kg/day, approximately >50 times the human daily dose. The number of early resorptions increased in both species. There was no evidence of teratogenic effects.

8.2 Lactation

Risk Summary

There is no information regarding the presence of heparin in human milk, the effects on the breastfed child, or the effects on milk production. Due to its large molecular weight, heparin is not likely to be excreted in human milk.

The developmental and health benefits of breastfeeding should be considered along with the mother's clinical need for HEPARIN SODIUM IN SODIUM CHLORIDE INJECTION and any potential adverse effects on the breastfed child from HEPARIN SODIUM IN SODIUM CHLORIDE INJECTION or from the underlying maternal condition [see Use in Specific Populations (8.4)].

8.4 Pediatric Use

Safety and effectiveness in pediatric patients have not been established.

8.5 Geriatric Use

A higher incidence of bleeding has been reported in patients over 60 years of age, especially women [see Warnings and Precautions (5.1)].

10 OVERDOSAGE

Bleeding is the chief sign of heparin overdosage.

Neutralization of heparin effect:

When clinical circumstances (bleeding) require reversal of heparinization, protamine sulfate (1% solution) by slow infusion will neutralize heparin sodium. No more than 50 mg should be administered, very slowly, in any 10 minute period. Each mg of protamine sulfate neutralizes approximately 100 USP Heparin Units. The amount of protamine required decreases over time as heparin is metabolized. Although the metabolism of heparin is complex, it may, for the purpose of choosing a protamine dose, be assumed to have a half-life of about 1/2 hour after intravenous injection.

Because fatal reactions often resembling anaphylaxis have been reported, protamine sulfate should be given only when resuscitation techniques and treatment of anaphylactoid shock are readily available.

For additional information, consult the prescribing information for Protamine Sulfate Injection, USP.

11 DESCRIPTION

Intravenous solutions with heparin sodium (derived from porcine intestinal mucosa) are sterile, nonpyrogenic fluids for intravenous administration. Each 100 mL contains heparin sodium 200 USP Units; sodium chloride, 0.9 g; citric acid, anhydrous, 37 mg and dibasic sodium phosphate, heptahydrate, 430 mg added as buffers. Each liter contains the following electrolytes: Sodium 186.1 mEq; phosphate (as HPO4=) 32.1 mEq; citrate 5.8 mEq; and chloride 153.9 mEq. Osmolar concentration, 358 mOsmol/liter (calc.); pH 7.0 (5.0 – 7.5).

Heparin Sodium, USP is a heterogeneous group of straight-chain anionic mucopolysaccharides, called glycosaminoglycans having anticoagulant properties. Although others may be present, the main sugars occurring in heparin are: (1) α-L-iduronic acid 2-sulfate, (2) 2-deoxy-2-sulfamino-α-D-glucose-6- sulfate, (3) β-D-glucuronic acid, (4) 2-acetamido-2-deoxy-α-D-glucose, and (5) α-L-iduronic acid.

These sugars are present in decreasing amounts, usually in the order (2) > (1) > (4) > (3) > (5), and are joined by glycosidic linkages, forming polymers of varying sizes. Heparin is strongly acidic because of its content of covalently linked sulfate and carboxylic acid groups. In heparin sodium, the acidic protons of the sulfate units are partially replaced by sodium ions. The potency is determined by a biological assay using a USP reference standard based on units of heparin activity per milligram.

Structure of Heparin Sodium (representative subunits):

Sodium Chloride, USP is chemically designated NaCl, a white crystalline compound freely soluble in water.

Dibasic Sodium Phosphate, USP (Heptahydrate), is chemically designated (Na2HPO4 7H2O), colorless or white granular salt freely soluble in water.

Citric Acid, USP, anhydrous is chemically designated C6H8O7, colorless, translucent crystals or white crystalline powder very soluble in water. It has the following structural formula:

Water for Injection, USP is chemically designated H2O.

The freeflex® container closure system is not made from natural rubber latex, is Non-PVC and Non-DEHP. Water can permeate from inside the container into the overwrap but not in amounts sufficient to affect the solution significantly. Solutions inside the plastic container also can leach out certain of its chemical components in very small amounts before the expiration period is attained. However, the safety of the plastic has been confirmed by tests in animals according to USP biological standards for plastic containers.

12 CLINICAL PHARMACOLOGY

12.1 Mechanism of Action

Heparin interacts with the naturally occurring plasma protein, Antithrombin III, to induce a conformational change, which markedly enhances the serine protease activity of Antithrombin II, thereby inhibiting the activated coagulation factors involved in the closing sequence, particularly Xa and IIa. Small amounts of heparin inhibit Factor Xa, and larger amounts inhibit thrombin (Factor IIa).

Heparin also prevents the formation of a stable fibrin clot by inhibiting the activation of the fibrin stabilizing factor. Heparin does not have fibrinolytic activity; therefore, it will not lyse existing clots.

12.2 Pharmacodynamics

Various times (activated clotting time, activated partial thromboplastin time, prothrombin time, whole blood clotting time) are prolonged by full therapeutic doses of heparin; in most cases, they are not measurably affected by low doses of heparin. Bleeding time is usually unaffected by heparin.

12.3 Pharmacokinetics

Absorption

Heparin is not absorbed through the gastrointestinal tract and therefore administered via parenteral route. Peak plasma concentration and the onset of action are achieved immediately after intravenous administration.

Distribution

Heparin is highly bound to antithrombin, fibrinogens, globulins, serum proteases and lipoproteins. The volume of distribution is 0.07 L/kg.

Elimination

Metabolism

Heparin does not undergo enzymatic degradation.

Excretion

Heparin is mainly cleared from the circulation by liver and reticuloendothelial cells mediated uptake into extravascular space. Heparin undergoes biphasic clearance, a) rapid saturable clearance (zero order process due to binding to proteins, endothelial cells and macrophage) and b) slower first order elimination. The plasma half-life is dose-dependent and it ranges from 0.5 to 2 h.

Specific Populations

Geriatric Patients

Patients over 60 years of age, following similar doses of heparin, may have higher plasma levels of heparin and longer activated partial thromboplastin times (APTTs) compared with patients under 60 years of age [see Use in Specific Populations (8.5)].

13 NONCLINICAL TOXICOLOGY

13.1 Carcinogenesis, Mutagenesis, Impairment of Fertility

No long term studies in animals have been performed to evaluate carcinogenic potential of heparin. Also, no reproduction studies in animals have been performed concerning mutagenesis or impairment of fertility.

16 HOW SUPPLIED/STORAGE AND HANDLING

Intravenous solutions with heparin sodium are available in single-dose containers as follows:

Product Code | Unit of Sale | Strength | Unit of Use
519077 | NDC 63323-519-77 Unit of 24 | Heparin Sodium 1,000 USP Units per 500 mL (2 USP Units per mL) in 0.9% Sodium Chloride | NDC 63323-519-02 500 mL freeflex® bag
519100 | NDC 63323-519-10 Unit of 12 | Heparin Sodium 2,000 USP Units per 1,000 mL (2 USP Units per mL) in 0.9% Sodium Chloride | NDC 63323-519-01 1,000 mL freeflex® bag

Store at 20 to 25°C (68 to 77°F). [See USP Controlled Room Temperature.] Protect from freezing.

17 PATIENT COUNSELING INFORMATION

Hemorrhage

Inform patients that it may take them longer than usual to stop bleeding, that they may bruise and/or bleed more easily when they are treated with heparin, and that they should report any unusual bleeding or bruising to their physician. Hemorrhage can occur at virtually any site in patients receiving heparin. Fatal hemorrhages have occurred [see Warnings and Precautions (5.1)].

Prior to Surgery

Advise patients to inform physicians and dentists that they are receiving heparin before any surgery is scheduled [see Warnings and Precautions (5.1)].

Heparin-Induced Thrombocytopenia

Inform patients of the risk of heparin-induced thrombocytopenia (HIT). HIT may progress to the development of venous and arterial thromboses, a condition known as heparin-induced thrombocytopenia and thrombosis (HITT). HIT can occur up to several weeks after the discontinuation of heparin therapy [see Warnings and Precautions (5.2)].

Hypersensitivity

Inform patients that generalized hypersensitivity reactions have been reported. Necrosis of the skin has been reported at the site of subcutaneous injection of heparin [see Warnings and Precautions (5.5), Adverse Reactions (6.1)].

Other Medications

Because of the risk of hemorrhage, advise patients to inform their physicians and dentists of all medications they are taking, including non-prescription medications, and before starting any new medication [see Drug Interactions (7)].

Manufactured for:

Lake Zurich, IL 60047
Made in Norway
www.fresenius-kabi.com/us
451480
Issued: 5/2020

PACKAGE LABEL

PACKAGE LABEL- PRINCIPAL DISPLAY PANEL – Heparin Sodium 500 mL Bag Label

NDC 63323-519-02

Heparin
Sodium

in 0.9% Sodium Chloride

Injection

1,000 USP units
per 500 mL
(2 USP units per mL)

For intravenous use
only.

Single Dose Container.

Discard unused
portion.

Rx only

PACKAGE LABEL

PACKAGE LABEL- PRINCIPAL DISPLAY PANEL – Heparin Sodium 1000 mL Bag Label

NDC 63323-519-01

Heparin
Sodium

in 0.9% Sodium Chloride

Injection

2,000 USP units
per 1,000 mL
(2 USP units per mL)

For intravenous use
only.

Single Dose Container.

Discard unused
portion.

Rx only

PACKAGE LABEL

PACKAGE LABEL – PRINCIPAL DISPLAY – Heparin Sodium 500 mL Shipper Label

NDC 63323-519-77 519077

Heparin Sodium

in 0.9% Sodium Chloride Injection

1,000 USP units

per 500 mL (2 USP units per mL)

PACKAGE LABEL

PACKAGE LABEL – PRINCIPAL DISPLAY – Heparin Sodium 1,000 mL Shipper Label

NDC 63323-519-10 519100

Heparin Sodium

in 0.9% Sodium Chloride Injection

2,000 USP units per 1,000 mL (2 USP units per mL)